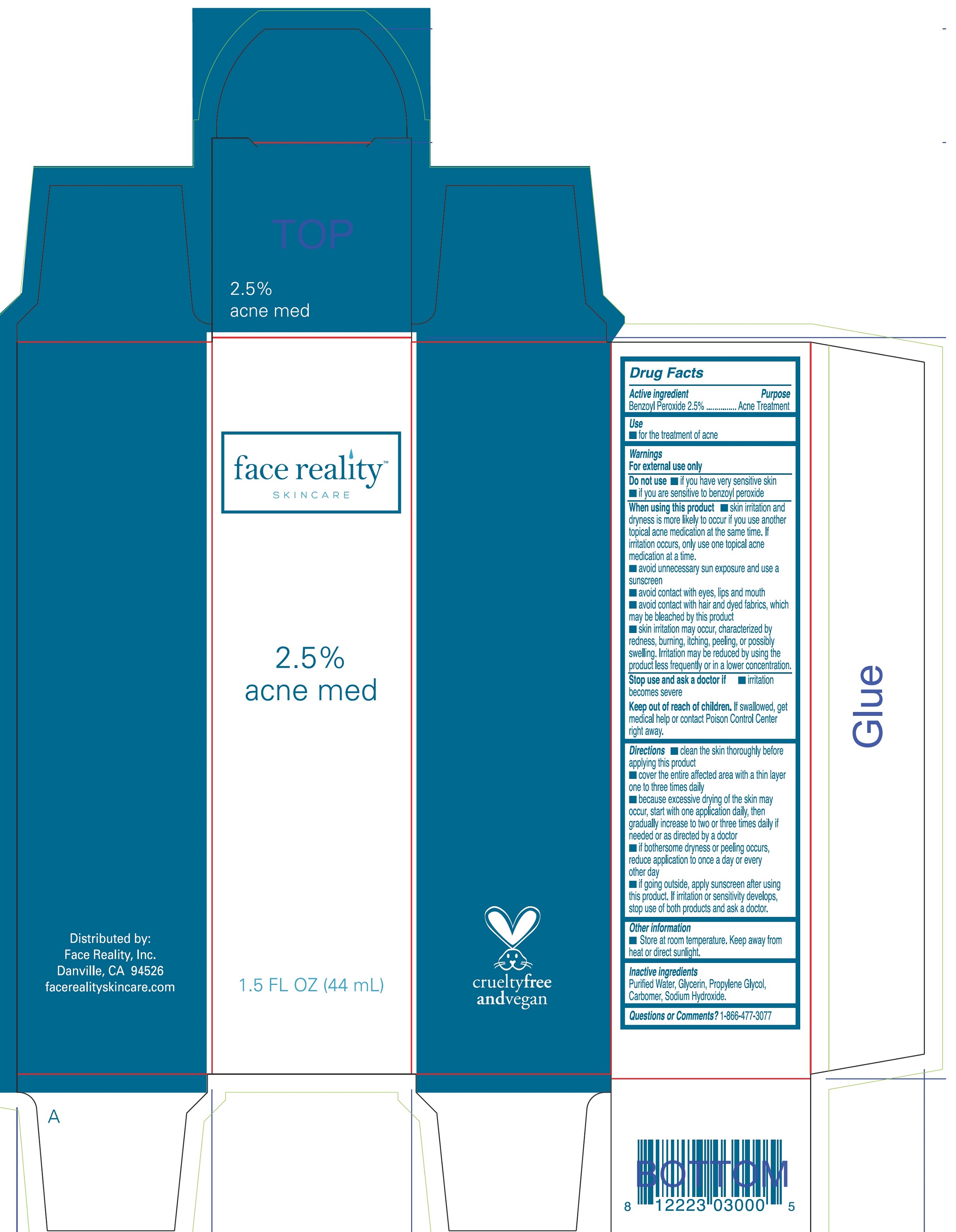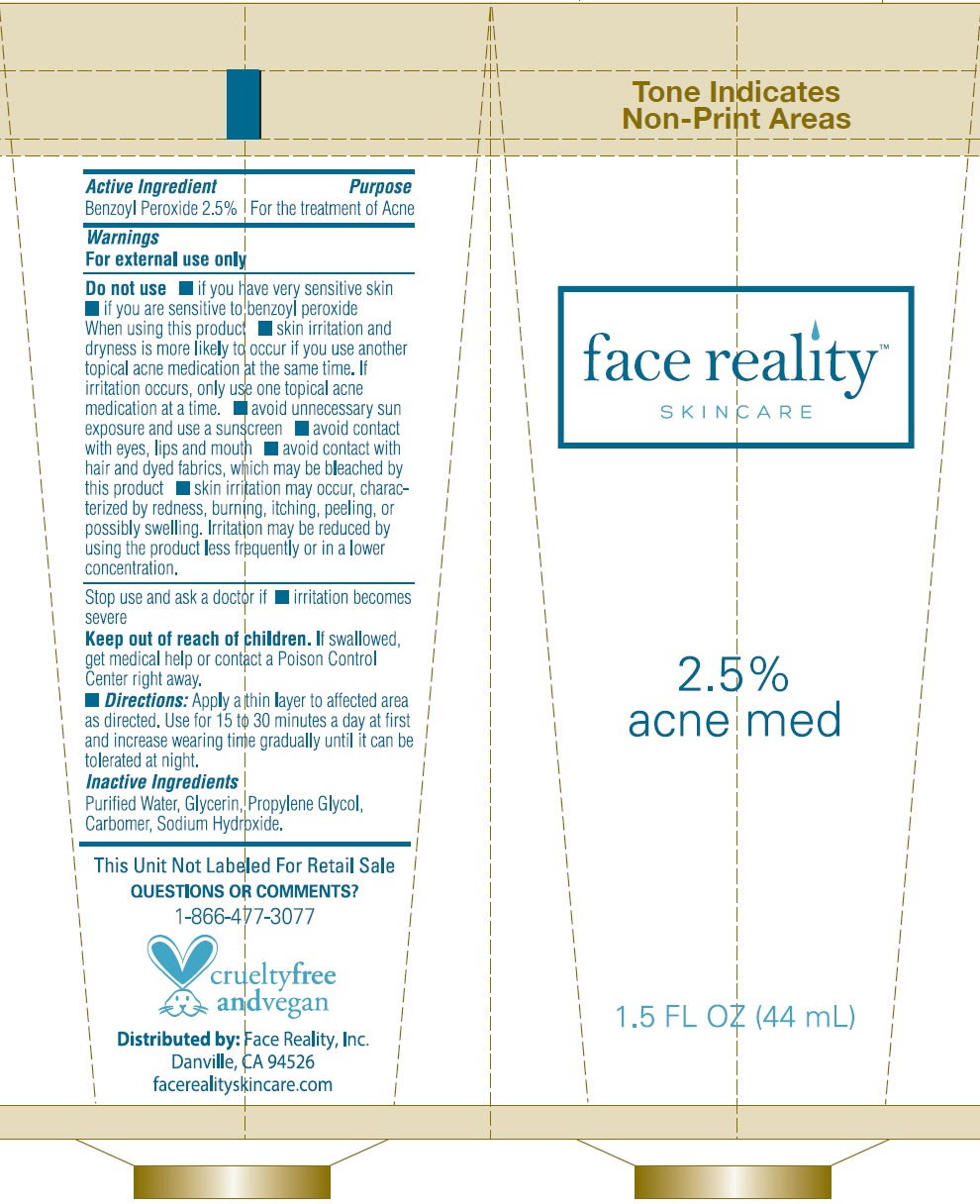 DRUG LABEL: 2.5 Acne Med
NDC: 70707-152 | Form: GEL
Manufacturer: Face Reality, Inc.
Category: otc | Type: HUMAN OTC DRUG LABEL
Date: 20240605

ACTIVE INGREDIENTS: BENZOYL PEROXIDE 25 mg/1 mL
INACTIVE INGREDIENTS: WATER; GLYCERIN; PROPYLENE GLYCOL; CARBOMER HOMOPOLYMER, UNSPECIFIED TYPE; SODIUM HYDROXIDE

2.5 % Acne Med

Active ingredient

Benzoyl Peroxide 2.5%

Purpose

Acne Treatment

Use

- for the treatment of acne

Warnings

For external use only

Do not use

- if you have very sensitive skin
- if you are sensitive to benzoyl peroxide

When using this product

- skin irritation and dryness is more likely to occur if you use another topical acne medication at the same time. If irritation occurs, only use one topical acne medication at a time.
- avoid unnecessary sun exposure and use a sunscreen
- avoid contact with eyes, lips and mouth
- avoid contact with hair and dyed fabrics, which may be bleached by this product
- skin irritation may occur, characterized by redness, burning, itching, peeling, or possibly swelling. Irritation may be reduced by using the product less frequently or in a lower concentration.

Stop use and ask a doctor if

- irritation becomes severe

Keep out of reach of children.

If swallowed, get medical help or contact Poison Control Center right away.

Directions

- clean the skin thoroughly before applying this product
- cover the entire affected area with a thin layer one or three times daily
- because excessive drying of the skin may occur, start with one application daily, then gradually increase to two or three times daily if needed or as directed by a doctor
- if bothersome dryness or peeling occurs, reduce application to once a day or every other day
- if going outside, apply sunscreen after using this product. If irritation or sensitivity develops, stop use of both products and ask a doctor.

Other information

- Store at room temperature. Keep away from heat or direct sunlight.

Inactive ingredients

Purified Water, Glycerin, Propylene Glycol, Carbomer, Sodium Hydroxide.

Questions or Comments?

1-866-477-3077